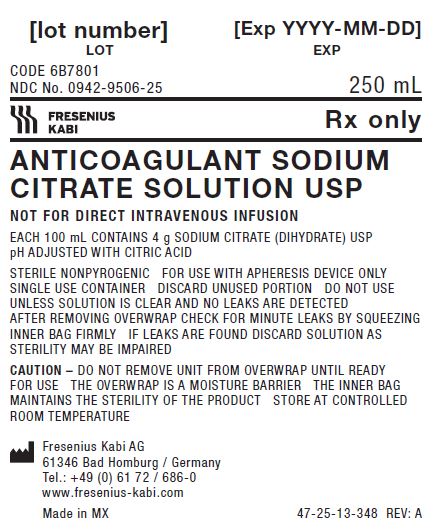 DRUG LABEL: Sodium Citrate Blood-Pack Units, (PL 146 Plastic)
NDC: 0942-9506 | Form: SOLUTION
Manufacturer: Fenwal, Inc.
Category: prescription | Type: HUMAN PRESCRIPTION DRUG LABEL
Date: 20221107

ACTIVE INGREDIENTS: TRISODIUM CITRATE DIHYDRATE 4 g/100 mL
INACTIVE INGREDIENTS: CITRIC ACID MONOHYDRATE

Anticoagulant Sodium Citrate Solution USP

A standalone direction insert does not exist for this product.

PACKAGE/LABEL PRINCIPAL DISPLAY PANEL

CODE 6B7801
NDC 0942-9506-25
250mL

Fresenius Kabi Rx only

ANTICOAGULANT SODIUM CITRATE SOLUTION USP

NOT FOR DIRECT INTRAVENOUS INFUSION
EACH 100 mL CONTAINS 4 g SODIUM CITRATE (DIHYDRATE) USP
pH ADJUSTED WITH CITRIC ACID
STERILE NONPYROGENIC FOR USE WITH APHERESIS DEVICE ONLY
SINGLE USE CONTAINER DISCARD UNUSED PORTION DO NOT USE
UNLESS SOLUTION IS CLEAR AND NO LEAKS ARE DETECTED
AFTER REMOVING OVERWRAP CHECK FOR MINUTE LEAKS BY SQUEEZING
INNER BAG FIRMLY IF LEAKS ARE FOUND DISCARD SOLUTION AS
STERILITY MAY BE IMPAIRED
CAUTION – DO NOT REMOVE UNIT FROM OVERWRAP UNTIL READY
FOR USE THE OVERWRAP IS A MOISTURE BARRIER THE INNER BAG
MAINTAINS THE STERILITY OF THE PRODUCT STORE AT CONTROLLED
ROOM TEMPERATURE
FRESENIUS KABI AG
61346 BAD HOMBURG / GERMANY

TEL.: +49 (0)6172 686-0
www.fresenius-kabi.com
Made in MX 47-25-13-348 REV: A